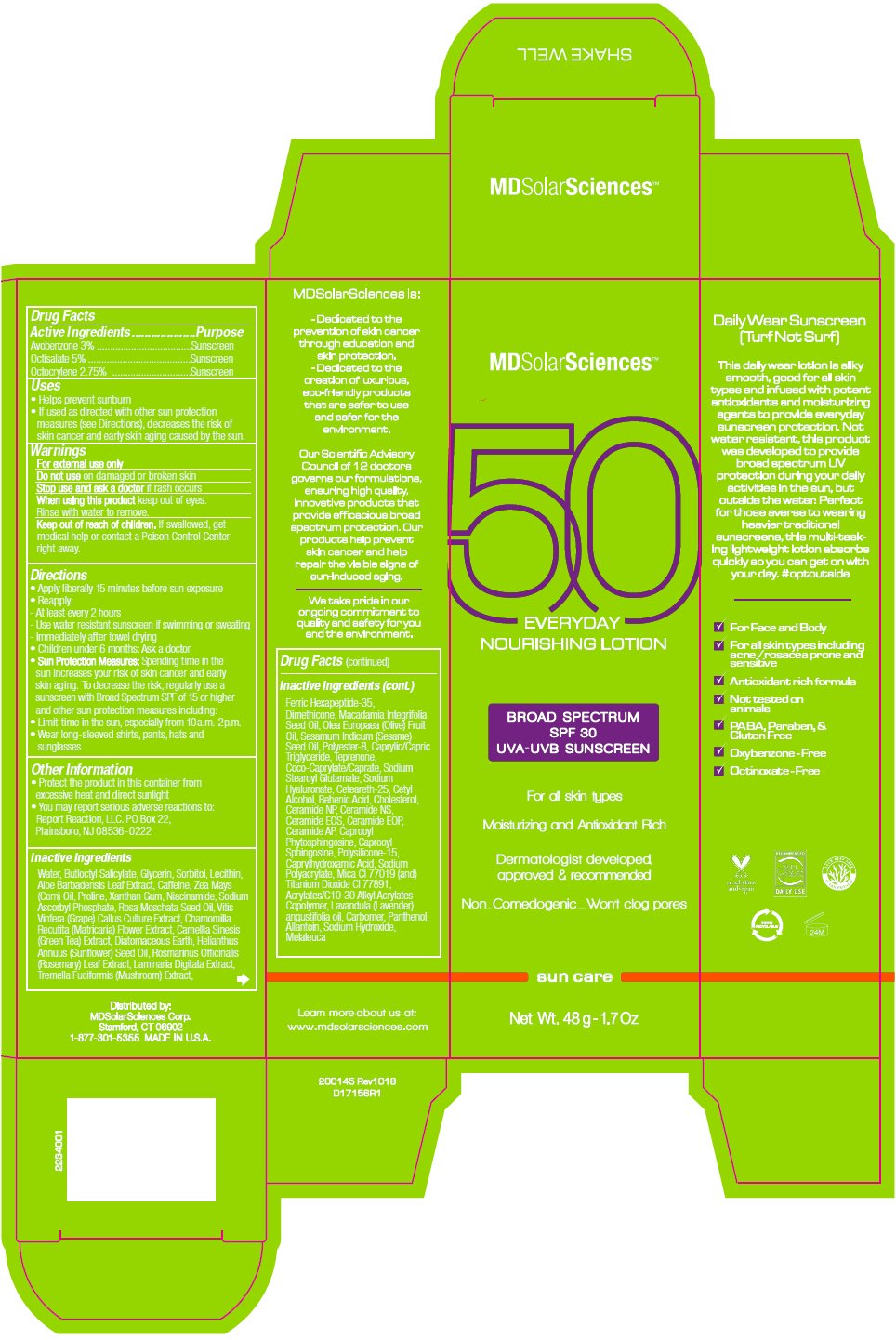 DRUG LABEL: Everyday Nourishing
NDC: 49358-562 | Form: LOTION
Manufacturer: MDSolarSciences
Category: otc | Type: HUMAN OTC DRUG LABEL
Date: 20190805

ACTIVE INGREDIENTS: Avobenzone 30 mg/1 mL; Octisalate 50 mg/1 mL; Octocrylene 27.5 mg/1 mL
INACTIVE INGREDIENTS: Water; Butyloctyl Salicylate; Coco-Caprylate/Caprate; Glycerin; Sorbitol; HYDROGENATED SOYBEAN LECITHIN; ALOE VERA LEAF; Caffeine; CORN OIL; Proline; Xanthan Gum; Sodium Ascorbyl Phosphate; Rosa Moschata Seed Oil; Niacinamide; VITIS VINIFERA SEED; CHAMOMILE; GREEN TEA LEAF; Diatomaceous Earth; HELIANTHUS ANNUUS FLOWERING TOP; ROSEMARY; LAMINARIA DIGITATA; TREMELLA FUCIFORMIS FRUITING BODY; ACETYL HEXAPEPTIDE-8; SESAME OIL; MACADAMIA OIL; OLIVE OIL; Polysilicone-15; HYALURONATE SODIUM; Dimethicone; Ceteareth-25; Cetyl Alcohol; Behenic Acid; Cholesterol; Ceramide NP; CERAMIDE NG; 3-DEHYDROXY CERAMIDE 1; CERAMIDE 9; Ceramide AP; CAPROOYL TETRAPEPTIDE-3; N-HEXANOYLSPHINGOSINE; MEDIUM-CHAIN TRIGLYCERIDES; Teprenone; Sodium Stearoyl Glutamate; POLYESTER-8 (1400 MW, CYANODIPHENYLPROPENOYL CAPPED); Caprylhydroxamic Acid; Caprylyl Glycol; CARBOMER HOMOPOLYMER TYPE C (ALLYL PENTAERYTHRITOL CROSSLINKED); CARBOMER INTERPOLYMER TYPE A (ALLYL SUCROSE CROSSLINKED); Allantoin; Panthenol; SODIUM POLYACRYLATE (8000 MW); Mica; TEA TREE OIL; LAVENDER OIL; Sodium Hydroxide

Everyday Nourishing Lotion 2.5oz
Broad Spectrum SPF30 Sunscreen UVA-UVB Suncreen

Drug Facts

ACTIVE INGREDIENT

Active Ingredients | Purpose
Avobenzone 3% | Sunscreen
Octisalate 5% | Sunscreen
Octocrylene 2.75% | Sunscreen

Uses

- Helps prevent sunburn
- If used as directed with other sun protection measures (see Directions), decreases the risk of skin cancer and early skin aging caused by the sun.

Warnings

For external use only

Do not use on damaged or broken skin

Stop use and ask a doctor if rash occurs

When using this product keep out of eyes. Rinse with water to remove.

Keep out of reach of children. If swallowed, get medical help or contact a Poison Control Center right away.

Directions

- Apply liberally 15 minutes before sun exposure
- Reapply:
  - At least every 2 hours
  - Use water resistant sunscreen if swimming or sweating
  - Immediately after towel drying
- Children under 6 months: Ask a doctor
- Sun Protection Measures: Spending time in the sun increases your risk of skin cancer and early skin aging. To decrease the risk, regularly use a sunscreen with Broad Spectrum SPF of 15 or higher and other sun protection measures including:
- Limit time in the sun, especially from 10a.m.- 2p.m.
- Wear long-sleeved shirts, pants, hats and sunglasses

Other Information

- Protect the product in this container from excessive heat and direct sunlight
- You may report serious adverse reactions to: Report Reaction, LLC. PO Box 22, Plainsboro, NJ 08536-0222

Inactive Ingredients

Water, Butloctyl Salicylate, Glycerin, Sorbitol, Lecithin, Aloe Barbadensis Leaf Extract, Caffeine, Zea Mays (Corn) Oil, Proline, Xanthan Gum, Niacinamide, Sodium Ascorbyl Phosphate, Rosa Moschata Seed Oil, Vitis Vinfera (Grape) Callus Culture Extract, Chamomilla Recutita (Matricaria) Flower Extract, Camellia Sinesis (Green Tea) Extract, Diatomaceous Earth, Helianthus Annuus (Sunflower) Seed Oil, Rosmarinus Officinalis (Rosemary) Leaf Extract, Laminaria Digitata Extract, Tremella Fuciformis (Mushroom) Extract, Ferric Hexapeptide-35, Dimethicone, Macadamia Integrifolia Seed Oil, Olea Europaea (Olive) Fruit Oil, Sesamum Indicum (Sesame) Seed Oil, Polyester-8, Caprylic/Capric Triglyceride, Teprenone, Coco-Caprylate/Caprate, Sodium Stearoyl Glutamate, Sodium Hyaluronate, Ceteareth-25, Cetyl Alcohol, Behenic Acid, Cholesterol, Ceramide NP, Ceramide NS, Ceramide EOS, Ceramide EOP, Ceramide AP, Caprooyl Phytosphingosine, Caprooyl Sphingosine, Polysilicone-15, Caprylhydroxamic Acid, Sodium Polyacrylate, Mica CI 77019 (and) Titanium Dioxide CI 77891, Acrylates/C10-30 Alkyl Acrylates Copolymer, Lavandula (Lavender) angustifolia oil, Carbomer, Panthenol, Allantoin, Sodium Hydroxide, Melaleuca

Distributed by:
MDSolarSciences Corp.
Stamford, CT 06902

PRINCIPAL DISPLAY PANEL - 71 mL Tube Carton

MDSolarSciences™

50
EVERYDAY
NOURISHING LOTION

BROAD SPECTRUM
SPF 30
UVA-UVB SUNSCREEN

For all skin types

Moisturizing and Antioxidant Rich

Dermatologist developed,
approved & recommended

Non-Comedogenic – Won't clog pores

sun care

Net Wt. 48 g -1.7Oz